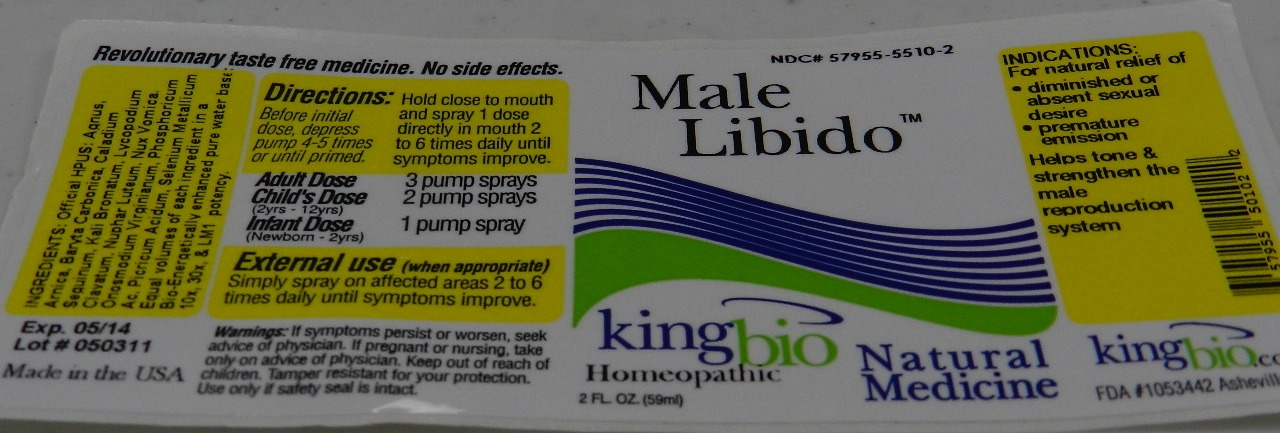 DRUG LABEL: Male Libido
NDC: 57955-5510 | Form: LIQUID
Manufacturer: King Bio Inc
Category: homeopathic | Type: HUMAN OTC DRUG LABEL
Date: 20110622

ACTIVE INGREDIENTS: CHASTE TREE 10 [hp_X]/1 mL; ARNICA MONTANA 10 [hp_X]/1 mL; BARIUM CARBONATE 10 [hp_X]/1 mL; DIEFFENBACHIA SEGUINE 10 [hp_X]/1 mL; POTASSIUM BROMIDE 10 [hp_X]/1 mL; LYCOPODIUM CLAVATUM SPORE 10 [hp_X]/1 mL; NUPHAR LUTEUM ROOT 10 [hp_X]/1 mL; STRYCHNOS NUX-VOMICA SEED 10 [hp_X]/1 mL; ONOSMODIUM VIRGINIANUM ROOT 10 [hp_X]/1 mL; PHOSPHORIC ACID 10 [hp_X]/1 mL; TRINITROPHENOL 10 [hp_X]/1 mL; SELENIUM 10 [hp_X]/1 mL
INACTIVE INGREDIENTS: WATER

Male Libido

OTC Active Ingredient for Male Libido

Active Ingredients:
Agnus Castus
Arnica Montana
Baryta Corbonica
Caladium Seguinum
Kali Bromatum
Lycopium Clavatum
Nux Vomica
Onosmodium Virginianum
Phosphoricum Acidum
Picricum Acidum
Selenium Metallicum
Reference image male libido.jpg

Inactive Ingredients for Male Libido

Bio-Energetically enhanced pure water base

Reference image male libido.jpg

Dosage and Administration for Male Libido

Directions:

Hold close to mouth and spray 1 dose directly in mouth 2 to 6 times daily until symptoms improve.

Adult Dose: 3 pump sprays

Child's Dose: 2 pump sprays (2yrs-12yrs)

Infant Dose: 1 pump sprays (newborn-2yrs)

External Use: (when appropriate) Simply spray on affected areas 2 to 6 times daily until symptoms improve.

Reference image of male libido.jpg

OTC Purpose for Male Libido

For natural relief of diminished or absent sexual desire, premature emission.

Helps tone and strengthen the male reproduction system.

Reference image of male libido.jpg

Warnings for Male Libido

Warnings: If symptoms persist or worsen, seek advice of physician. If pregnant or nursing, take only on advice of a physician. Keep out of reach of children. Tamper resistant for your protection. Use only if seal is intact.

Reference image of male libido.jpg

OTC Keep out of reach of children for Male Libido

Keep out of reach of children. If pregnant or nursing, take only on advice of a physician.

Reference image of male libido.jpg

Indications and usage for Male Libido

Indications: For natural relief of

- diminished or absent sexual desire
- premature emission
- Helps tone and strengthen the male reproduction system

Reference image of male libido.jpg

Package Label Principal display Panel for Male Libido

Reference image of male libido.jpg